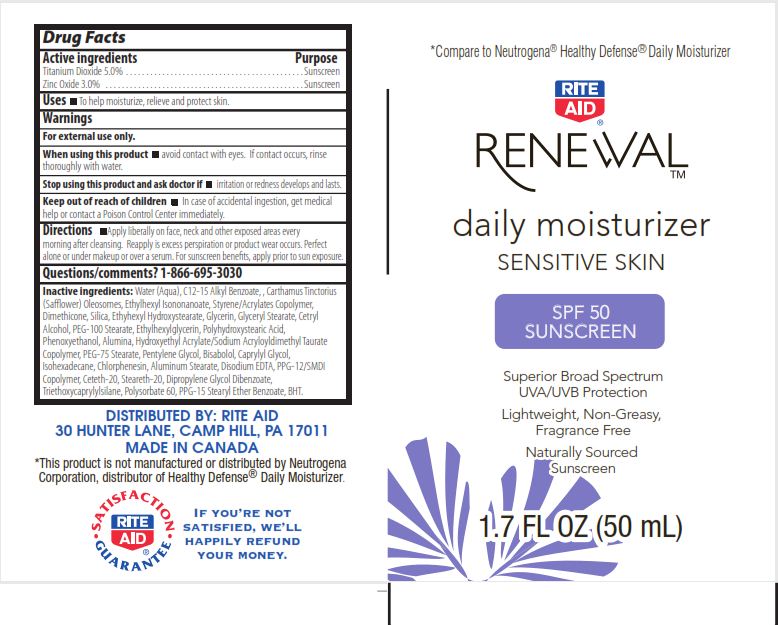 DRUG LABEL: RENEWAL DAILY MOISTURIZER SENSITIVE SKIN
NDC: 11822-3420 | Form: LOTION
Manufacturer: RITE AID CORPORATION
Category: otc | Type: HUMAN OTC DRUG LABEL
Date: 20110721

ACTIVE INGREDIENTS: TITANIUM DIOXIDE 5 mL/100 mL; ZINC OXIDE 3 mL/100 mL
INACTIVE INGREDIENTS: WATER; ALKYL (C12-15) BENZOATE; CARTHAMUS TINCTORIUS (SAFFLOWER) OLEOSOMES; ETHYLHEXYL ISONONANOATE; SILICON DIOXIDE; ETHYLHEXYL HYDROXYSTEARATE; GLYCERIN; GLYCERYL MONOSTEARATE; CETYL ALCOHOL; PEG-100 STEARATE; ETHYLHEXYLGLYCERIN; POLYHYDROXYSTEARIC ACID (2300 MW); ALUMINUM OXIDE; PEG-75 STEARATE; PENTYLENE GLYCOL; .ALPHA.-BISABOLOL, (+/-)-; CAPRYLYL GLYCOL; ISOHEXADECANE; CHLORPHENESIN; ALUMINUM STEARATE; EDETATE DISODIUM; CETETH-20; STEARETH-20; TRIETHOXYCAPRYLYLSILANE; POLYSORBATE 60; BUTYLATED HYDROXYTOLUENE

DRUG FACTS

ACTIVE INGREDIENTS

TITANIUM DIOXIDE 5.0%

ZINC OXIDE 3.0%

PURPOSE

SUNSCREEN

SUNSCREEN

USES

TO HELP MOISTURIZE, RELIEVE AND PROTECT SKIN.

WARNINGS

FOR EXTERNAL USE ONLY.

WHEN USING THIS PRODUCT

AVOID CONTACT WITH EYES. IF CONTACT OCCURS, RINSE THOROUGHLY WITH WATER.

STOP USING THIS PRODUCT AND ASK DOCTOR IF

IRRITATION OR REDNESS DEVELOPS AND LASTS.

KEEP OUT OF REACH OF CHILDREN

Enter section text here

DIRECTIONS

APPLY LIBERALLY ON FACE, NECK AND OTHER EXPOSED AREAS EVERY MORNING AFTER CLEANSING. REAPPLY IF EXCESS PERSPIRATION OR PRODUCT WEARS OCCURS. PERFECT ALONE OR UNDER MAKEUP OR OVER A SERUM. FOR SUNSCREEN BENEFITS, APPLY PRIOR TO SUN EXPOSURE.

QUESTIONS/COMMENTS?

1-866-695-3030

INACTIVE INGREDIENTS

WATER, C12-15 ALKYL BENZOATE, CARTHAMUS TINCTORIUS (SAFFLOWER) OLEOSOMES, ETHYLHEXYL ISONONANOATE, STYRENE/ACRYLATES COPOLYMER, DIMETHICONE, SILICA, ETHYHEXYL HYDROXYSTEARATE, GLYCERIN, GLYCERYL STEARATE, CETYL ALCOHOL, PEG-100 STEARATE, ETHYLHEXYLGLYCERIN, POLYHYDROXYSTEARIC ACID, PHENOXYETHANOL, ALUMINA, HYDROXYETHYL ACRYLATE/SODIUM ACRYLOYLDIMETHYL TAURATE COPOLYMER, PEG-75 STEARATE, PENTYLENE GLYCOL, BISABOLOL, CAPRYLYL GLYCOL, ISOHEXADECANE, CHLORPHENESIN, ALUMINUM STEARATE, DISODIUM EDTA, PPG-12/SMDI COPOLYMER, CETETH-20, STEARETH-20, DIPROPYLENE GLYCOL DIBENZOATE, TRIETHOXYCAPRYLYLSILANE, POLYSORBATE 60, PPG-15 STEARYL ETHER BENZOATE, BHT.